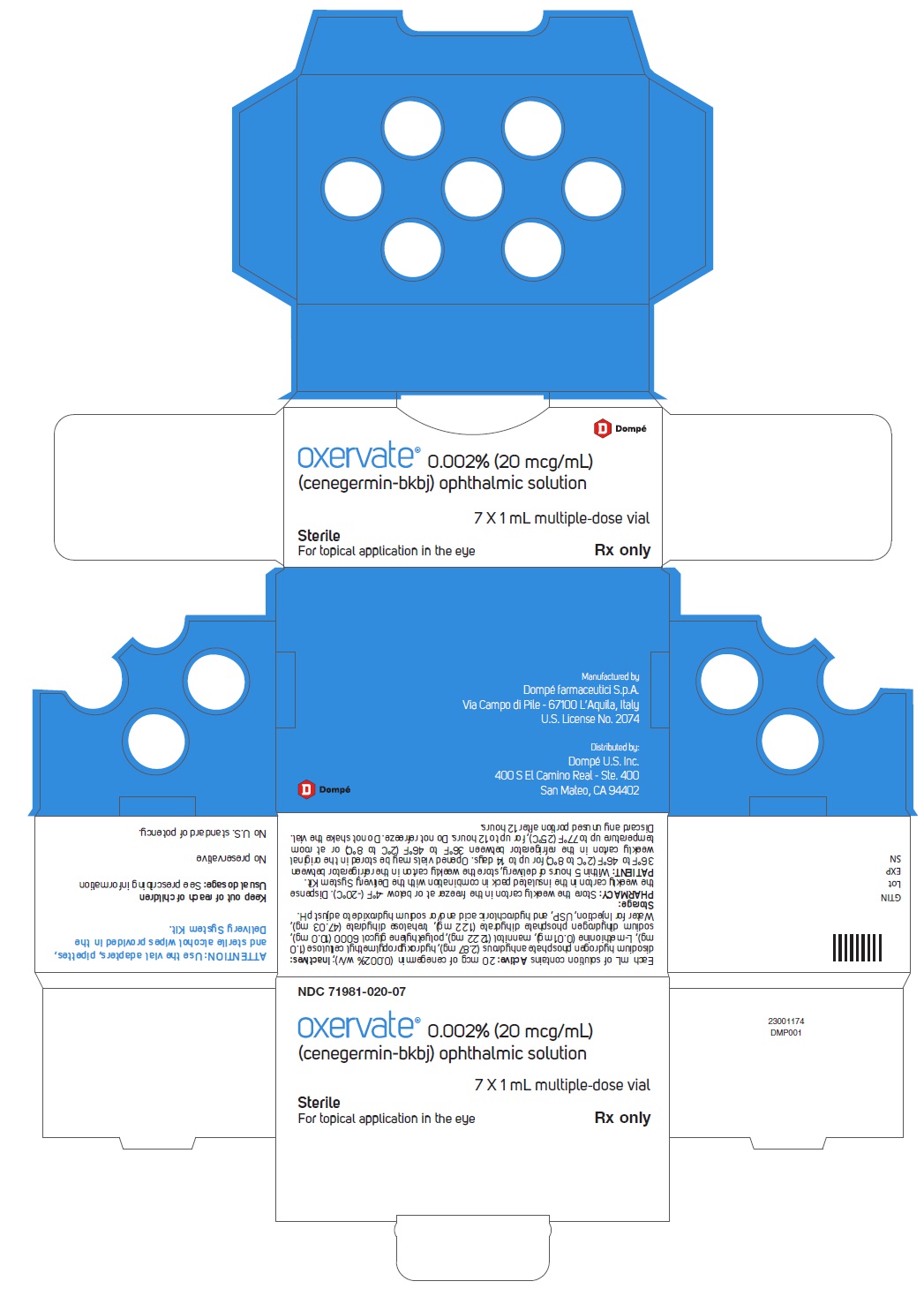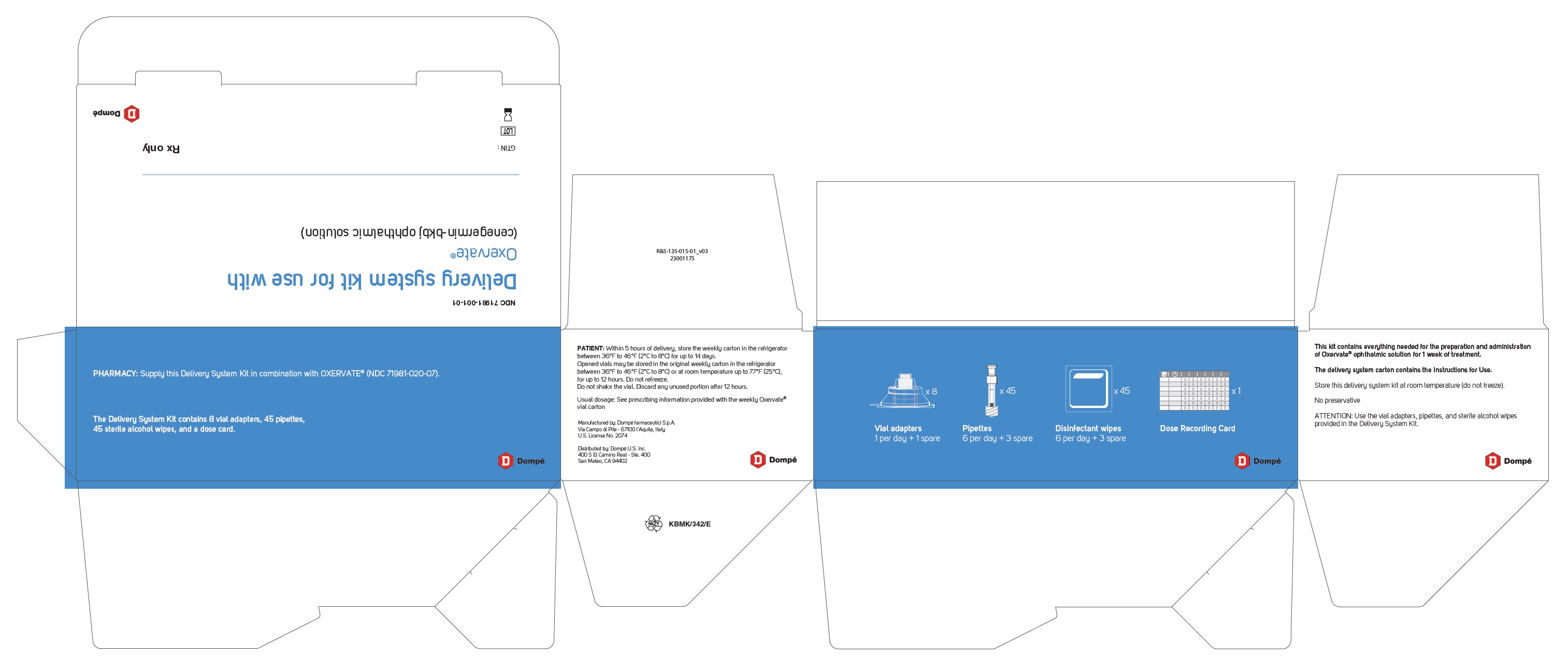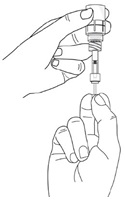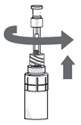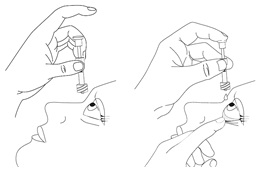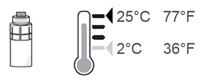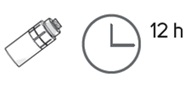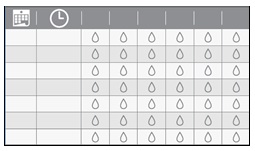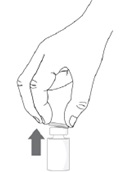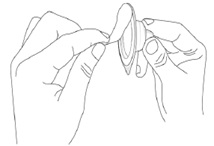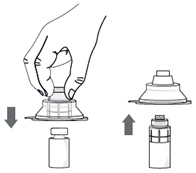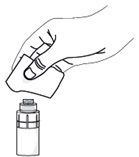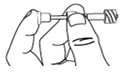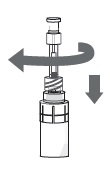 DRUG LABEL: OXERVATE
NDC: 71981-020 | Form: SOLUTION/ DROPS
Manufacturer: Dompé farmaceutici S.p.A.
Category: prescription | Type: HUMAN PRESCRIPTION DRUG LABEL
Date: 20250205

ACTIVE INGREDIENTS: CENEGERMIN 20 ug/1 mL
INACTIVE INGREDIENTS: SODIUM PHOSPHATE, DIBASIC, ANHYDROUS 2.87 mg/1 mL; HYPROMELLOSE, UNSPECIFIED 1.0 mg/1 mL; METHIONINE 0.01 mg/1 mL; MANNITOL 12.22 mg/1 mL; POLYETHYLENE GLYCOL 6000 10.0 mg/1 mL; SODIUM PHOSPHATE, MONOBASIC, DIHYDRATE 1.22 mg/1 mL; TREHALOSE DIHYDRATE 47.03 mg/1 mL; WATER; HYDROCHLORIC ACID; SODIUM HYDROXIDE; NITROGEN

HIGHLIGHTS OF PRESCRIBING INFORMATION

These highlights do not include all the information needed to use OXERVATE safely and effectively. See full prescribing information for OXERVATE.
OXERVATE® (cenegermin-bkbj) ophthalmic solution, for topical ophthalmic use
Initial U.S. Approval: 2018

1 INDICATIONS AND USAGE

OXERVATE is a recombinant human nerve growth factor indicated for the treatment of neurotrophic keratitis. (1)

2 DOSAGE AND ADMINISTRATION

One drop of OXERVATE in the affected eye(s), 6 times per day at 2-hour intervals, for eight weeks. (2.1)

3 DOSAGE FORMS AND STRENGTHS

Ophthalmic solution: cenegermin-bkbj 0.002% (20 mcg/mL) in a multiple-dose vial. (3)

4 CONTRAINDICATIONS

None. (4)

5 WARNINGS AND PRECAUTIONS

Patients should remove contact lenses before applying OXERVATE and wait 15 minutes after instillation of the dose before reinsertion. (5.1)

6 ADVERSE REACTIONS

The most common adverse reactions (incidence >5%) are eye pain, ocular hyperemia, eye inflammation and increased lacrimation. (6.1)

To report SUSPECTED ADVERSE REACTIONS, contact Dompé U.S. Inc. at 1-833-366-7387 or FDA at 1-800-FDA-1088 or www.fda.gov/medwatch.

FULL PRESCRIBING INFORMATION

1 INDICATIONS AND USAGE

OXERVATE® (cenegermin-bkbj) ophthalmic solution 0.002% is indicated for the treatment of neurotrophic keratitis.

2 DOSAGE AND ADMINISTRATION

2.1 General Dosing Information

Contact lenses should be removed before applying OXERVATE and may be reinserted 15 minutes after administration.

If a dose is missed, treatment should be continued as normal, at the next scheduled administration.

If more than one topical ophthalmic product is being used, administer the eye drops at least 15 minutes apart to avoid diluting products. Administer OXERVATE 15 minutes prior to using any eye ointment, gel or other viscous eye drops.

2.2 Recommended Dosage and Dose Administration

Instill one drop of OXERVATE in the affected eye(s), 6 times a day at 2-hour intervals for eight weeks.

2.3 Preparation for Administration

Remove the weekly carton(s) containing OXERVATE vials from the insulated pack and store it for up to 14 days in a refrigerator (no later than 5 hours from when you receive the medicine from your pharmacy). OXERVATE is stored in a freezer at the pharmacy. If treatment is started immediately after receiving the weekly carton, wait until the first vial is thawed (this could take up to 30 minutes when kept at room temperature up to 77°F (25°C)). Do not shake the vial.

Follow Steps 1 to 19 each day you use OXERVATE:

Take an individual vial of OXERVATE from the refrigerator in the morning and prepare it in the following way:

Step 1. Wash your hands.

Step 2. If you wear contact lenses, take them out before using OXERVATE.

Step 3. Remove the plastic flip-off cap from the vial.

Step 4. Peel-off the back of the vial adapter blister pack.

Step 5. Without removing the vial adapter from its blister pack, connect it to the vial by firmly pushing it down until it snaps into place over the neck of the vial. The spike of the vial adapter should pierce through the vial’s rubber stopper. After the vial adapter has been connected correctly, do not remove it from the vial.
Note: After the vial adapter is connected to the vial, OXERVATE can be stored in the refrigerator between 36°F to 46°F (2°C to 8°C) for up to 12 hours.
If needed, the OXERVATE with the connected vial adapter may be stored at room temperature up to 77°F (25°C).
Step 6. Remove and throw away the packaging of the vial adapter.

The multi-dose vial of OXERVATE is now ready for use (1 drop in the affected eye every 2 hours six times a day).

To withdraw and give each dose of OXERVATE, follow the Steps 7 to 19:

Step 7. Take a single sterile disinfectant wipe and gently clean the surface of the valve on the connector part of the vial adapter.
After cleaning, wait for about 1 minute to allow the valve to dry.

Step 8. Remove a pipette from its protective packaging.

Step 9. Screw the pipette (clockwise) into the connector part of the vial adapter.

Step 10. Make sure that the pipette plunger is pushed all the way down.

Step 11. Turn the vial upside-down with the pipette still connected. Gently pull the plunger until it stops, to draw the eye drop solution into the pipette. Make sure the plunger has reached the stop point.

Step 12. Check the pipette to make sure it contains the eye drop solution. Air bubbles may cause blockage and prevent the pipette from filling properly (especially the first time you withdraw the eye drop solution). If the pipette is empty, keep the vial with the connected pipette upside-down, push the plunger all the way in and pull it out again.

Step 13. After the pipette has been correctly filled, unscrew the pipette from the connector part of the vial adapter (counter-clockwise). Pull the pipette straight up to remove it.

Step 14.

- Sit or lie down to steady yourself when you instill OXERVATE.
- Holding the pipette, pointing down, between your middle finger and thumb, tilt your head back and position the pipette above your affected eye.
- With your other hand, pull down your lower eyelid, increasing the space between the inner eyelid and the eyeball (the conjunctival fornix).
- Gently push the plunger down until at least a drop is released into the conjunctival fornix.
- Make sure you do not touch your eye with the tip of the pipette.
- With your head still tilted back, blink a few times so that the medicine covers the surface of your eye.

Step 15. Throw away the used pipette right away after use, even if there is still some eye drop solution left in it.

Only use 1 pipette for each eye and each dose.

If you miss your eye and there is no longer any eye drop solution in the pipette, try again, using a new pipette and wipe (See Steps 7 to 14).

Step 16. After each use throughout the day, place the vial back in the refrigerator or keep it below 77°F (25°C) for the rest of the day, with the vial adapter still connected.

Step 17. Repeat from Step 7 to Step 16 every 2 hours 6 times a day, using a new sterile disinfectant wipe and a new pipette each time.

If you use drops in both eyes, repeat the above instructions for your other eye using a new pipette. You will need to use 2 vials each day.

Store the vial below 77°F (25°C) throughout the day. You can also store the vial in the refrigerator but do not freeze the vial.

Step 18. Throw away the used vial at the end of each day even if there is still some eye drop solution left in it. Throw away the vial no later than 12 hours from the time you connected the vial adapter to it even if there is eye solution still left in the vial.

Step 19. Track each time you instill an eye drop of OXERVATE on the weekly Dose Recording Card provided with the delivery system.

This will allow you to track your 6 doses each treatment day, the date of the first use of the weekly supply and the time of the vial opening (which is when you connect the vial adapter to the vial) during the week.

To make sure accurate dosing every 2 hours, you may want to set an alarm as a reminder for dosing.

3 DOSAGE FORMS AND STRENGTHS

Ophthalmic solution: cenegermin-bkbj 0.002% (20 mcg/mL) as a clear, colorless solution in a multiple dose vial.

4 CONTRAINDICATIONS

None.

5 WARNINGS AND PRECAUTIONS

5.1 Use with Contact Lens

Contact lenses should be removed before applying OXERVATE because the presence of a contact lens (either therapeutic or corrective) could theoretically limit the distribution of cenegermin-bkbj onto the area of the corneal lesion. Lenses may be reinserted 15 minutes after administration.

5.2 Eye Discomfort

OXERVATE may cause mild to moderate eye discomfort such as eye pain during treatment. The patient should be advised to contact their doctor if a more serious eye reaction occurs.

6 ADVERSE REACTIONS

6.1 Clinical Trials Experience

Because clinical studies are conducted under widely varying conditions, adverse reaction rates observed in the clinical studies of a drug cannot be directly compared to rates in the clinical studies of another drug and may not reflect the rates observed in practice.

In two clinical trials of patients with neurotrophic keratitis, a total of 101 patients received cenegermin-bkbj eye drops at 20 mcg/mL at a frequency of 6 times daily in the affected eye(s) for a duration of 8 weeks. The mean age of the population was 61 to 65 years of age (18 to 95). The majority of the treated patients were female (61%). The most common adverse reaction was eye pain following instillation which was reported in approximately 16% of patients. Eye pain may arise as corneal healing occurs.

Other adverse reactions occurring in 1% to 10% of OXERVATE patients included corneal deposits, foreign body sensation, ocular hyperemia, ocular inflammation, photophobia, tearing, and headache.

6.2 Postmarketing Experience

The following adverse reactions have been identified during postapproval use of OXERVATE. Because these reactions are reported voluntarily from a population of uncertain size, it is not always possible to reliably estimate their frequency or establish a causal relationship to drug exposure.

Eye disorders: eye irritation, blepharitis (including eyelid margin crusting and eyelid edema) and corneal neovascularization.

8 USE IN SPECIFIC POPULATIONS

8.1 Pregnancy

Risk Summary
There are no data from the use of OXERVATE in pregnant women to inform any drug associated risks.

Administration of cenegermin-bkbj to pregnant rats or rabbits during the period of organogenesis did not produce adverse fetal effects at clinically relevant doses. In a pre- and postnatal development study, administration of cenegermin-bkbj to pregnant rats throughout gestation and lactation did not produce adverse effects in offspring at clinically relevant doses.

Data
Animal Data
In embryofetal development studies, daily subcutaneous administration of cenegermin-bkbj to pregnant rats and rabbits throughout the period of organogenesis produced a slight increase in post-implantation loss at doses greater than or equal to 42 mcg/kg/day (267 times the MRHOD). A no observed adverse effect level (NOAEL) was not established for post-implantation loss in either species. In rats, hydrocephaly and ureter anomalies were observed each in one fetuses at 267 mcg/kg/day (1709 times the MRHOD). In rabbits, cardiovascular malformations, including ventricular and atrial septal defects, enlarged heart and aortic arch dilation were observed each in one fetuses at 83 mcg/kg/day (534 times the MRHOD). No fetal malformations were observed in rats and rabbits at doses of 133 mcg/kg/day and 42 mcg/kg/day, respectively.

In a pre- and postnatal development study, daily subcutaneous administration of cenegermin-bkbj to pregnant rats during the period of organogenesis and lactation did not affect parturition and was not associated with adverse toxicity in offspring at doses up to 267 mcg/kg/day.

In parental rats and rabbits, an immunogenic response to cenegermin-bkbj was observed. Given that cenegermin-bkbj is a heterologous protein in animals, this response may not be relevant to humans.

8.2 Lactation

Risk Summary
There are no data on the presence of OXERVATE in human milk, the effects on breastfed infant, or the effects on milk production. The developmental and health benefits of breastfeeding should be considered, along with the mother’s clinical need for OXERVATE, and any potential adverse effects on the breastfed infant from OXERVATE.

8.4 Pediatric Use

The safety and effectiveness of OXERVATE have been established in the pediatric population. Use of OXERVATE in this population is supported by evidence from adequate and well-controlled trials of OXERVATE in adults with additional safety data in pediatric patients from 2 years of age and older [see Clinical Studies (14)].

8.5 Geriatric Use

Of the total number of subjects in clinical studies of OXERVATE, 43.5% were 65 years old and over. No overall differences in safety or effectiveness were observed between elderly and younger adult patients.

11 DESCRIPTION

OXERVATE ophthalmic solution contains cenegermin-bkbj, a recombinant form of human nerve growth factor produced in Escherichia coli.

Cenegermin-bkbj contains 118 amino acids. Cenegermin-bkbj has a relative molecular mass of 13,266 Daltons and the following molecular formula: C583H908N166O173S8. OXERVATE (cenegermin-bkbj) is a clear, colorless sterile solution with a pH of 7.0-7.4 and osmolarity 280-320 mOsm/kg for topical ophthalmic use.

Each mL contains Active: 20 mcg of cenegermin (0.002% w/v); Inactives: disodium hydrogen phosphate anhydrous (2.87 mg), hydroxypropylmethyl cellulose (1.0 mg), L-methionine (0.01 mg), mannitol (12.22 mg), polyethylene glycol 6000 (10.0 mg), sodium dihydrogen phosphate dihydrate (1.22 mg), trehalose dihydrate (47.03 mg), Water for Injection, USP, and hydrochloric acid and/or sodium hydroxide to adjust pH. OXERVATE does not contain an anti-microbial preservative.

12 CLINICAL PHARMACOLOGY

12.1 Mechanism of Action

Nerve growth factor is an endogenous protein involved in the differentiation and maintenance of neurons, which acts through specific high-affinity (i.e., TrkA) and low-affinity (i.e. p75NTR) nerve growth factor receptors in the anterior segment of the eye to support corneal innervation and integrity.

12.2 Pharmacodynamics

No pharmacodynamic studies have been conducted in humans.

12.3 Pharmacokinetics

Systemic exposure to cenegermin-bkbj was evaluated by measuring serum nerve growth factor (NGF) concentrations in 20 healthy subjects who received single and multiple (up to six times a day) administration of one drop (35 μL) OXERVATE (0.70 μg of cenegermin-bkbj/administration). The study also included a placebo arm in 10 healthy subjects who received vehicle only.

At baseline/pre-dose, 17 out of the 20 subjects in the OXERVATE treatment arm had serum NGF concentrations below the limit of assay quantification (LLOQ <15 pg/mL) and the remaining three subjects had serum NGF concentrations ranging from 120 pg/mL to 503 pg/mL.

At baseline/pre-dose, 8 of the 10 subjects in the placebo arm had serum NGF concentrations below the limit of assay quantification (LLOQ <15 pg/mL) and the remaining two subjects had serum NGF concentrations ranging from 15 pg/mL to 116 pg/mL.

Overall, there was no apparent relationship between OXERVATE treatment and serum NGF concentrations.

13 NONCLINICAL TOXICOLOGY

13.1 Carcinogenesis, Mutagenesis, Impairment of Fertility

Carcinogenesis and Mutagenesis
Animal studies have not been conducted to determine the carcinogenic and mutagenic potential of cenegermin-bkbj.

Impairment of fertility
Daily subcutaneous administration of cenegermin-bkbj to male and female rats for at least 14 days prior mating, and at least 18 days post-coitum had no effect on fertility parameters in male or female rats at doses up to 267 mcg/kg/day (1709 times the MRHOD).

In general toxicology studies, subcutaneous and ocular administration of cenegermin-bkbj in females was associated with ovarian findings including persistent estrus, ovarian follicular cysts, atrophy/reduction of corpora lutea, and changes in ovarian weight at doses greater than or equal to 19 mcg/kg/day (119 times the MRHOD).

14 CLINICAL STUDIES

The efficacy and safety of OXERVATE for the treatment of neurotrophic keratitis was studied in a total of 151 patients, evaluated in two 8-week, randomized, multi-center, double-masked, vehicle-controlled studies. Patients were randomized to OXERVATE, cenegermin-bkbj 10 mcg/mL, or vehicle in Study NGF0212, and OXERVATE or vehicle in Study NGF0214 dosed 6 times daily in the affected eye(s) for 8 weeks. In study NGF0212, only patients with unilateral disease were enrolled, while in study NGF0214 patients with bilateral disease were treated bilaterally. The mean age was 61 to 65 years (18-95). The majority of patients were female (approximately 61%).

Table 1 below summarizes the results for complete corneal healing defined as absence of staining of the corneal lesion and no persistent staining in the rest of the cornea after 8 weeks of treatment.

Table 1. Percentage of Patients with Complete Corneal Healing at Week 8

Study | OXERVATE | Vehicle | Treatment Difference* (95% CI)
NGF0214 | 15/23 (65.2%) | 4/24 (16.7%) | 48.6% (24%, 73.1%)
NGF0212 | 36/50 (72.0%) | 17/51 (33.3%) | 38.7% (20.7%, 56.6%)
Patients without any post-baseline measurements were excluded from the analysis.
* p-value < 0.01 for both studies.

In patients who were healed after 8 weeks of treatment with OXERVATE, recurrences occurred in approximately 20% of patients in Study NGF0212 and 14% of patients in Study NGF0214.

The results of the mean change from baseline in corneal sensitivity inside the lesion after 8 weeks of treatment are summarized descriptively in Table 2. The mean changes in corneal sensitivity were not clinically significant in either study.

Table 2. Mean Corneal Sensitivity inside the Lesion: Baseline and Change from Baseline at Week 8

Study | Visit* | OXERVATE | Vehicle | Treatment Difference** (95% CI)
NGF0214 | Baseline | 0.8 (1.19) | 0.6 (0.70)
NGF0214 | Change from baseline at Week 8 | 1.6 (0.26) | 0.7 (0.25) | 0.9 (0.2, 1.7)
NGF0212 | Baseline | 1.1 (1.34) | 1.0 (1.19)
NGF0212 | Change from baseline at Week 8 | 1.1 (0.23) | 0.8 (0.23) | 0.3 (-0.4, 0.9)
Change from baseline in corneal sensitivity inside the lesion was analyzed using an analysis of covariance model adjusting for baseline values. Patients without any post-baseline measurements were excluded from the analysis.
*Mean (standard deviation) are presented at baseline; least squared means (standard error) are presented at Week 8
** NGF0214: OXERVATE, n = 21; Vehicle, n = 23
NGF0212: OXERVATE, n = 48; Vehicle, n = 47

16 HOW SUPPLIED/STORAGE AND HANDLING

OXERVATE (cenegermin-bkbj) ophthalmic solution, 0.002% (20 mcg/mL), is a sterile, clear, colorless solution in a multiple-dose vial, closed with a rubber stopper (not made with natural rubber latex), and an aluminum overseal with a polypropylene flip-off cap.

OXERVATE is supplied in weekly cartons containing 7 multiple-dose vials (NDC 71981-020-07). OXERVATE is dispensed to patients in an insulated pack and co-packaged with the Delivery System Kit (NDC 71981-001-01). The Delivery System Kit contains 8 vial adapters, 45 pipettes, 45 sterile disinfectant wipes, and 1 Dose Recording Card.

Pharmacy Storage
Store the weekly cartons containing OXERVATE vials in the freezer at or below -4°F (-20°C). Dispense the weekly carton(s) containing OXERVATE vials in an insulated pack in combination with the Delivery System Kit.

Patient Storage
Within 5 hours of delivery, store the weekly carton(s) containing OXERVATE vials in the refrigerator between 36°F to 46°F (2°C to 8°C) for up to 14 days. A vial opened for daily use may be stored in the original weekly carton in the refrigerator between 36°F to 46°F (2°C to 8°C) or at room temperature up to 77°F (25°C), for up to 12 hours [see Dosage and Administration (2.1)]. Do not refreeze the vials. Do not shake the vials. Discard the opened vial after 12 hours even if there is still some solution left inside.

17 PATIENT COUNSELING INFORMATION

Advise the patient to read the FDA-approved patient labeling (Patient Information and Instructions for Use).

Handling the Vials and the Delivery System
Advise patients that OXERVATE should be administered using the vial adapters, pipettes, and sterile disinfectant wipes provided in the Delivery System Kit and according to the instructions [see Dosage and Administration (2)]. One individual pipette should be used per application.

Use with Contact Lenses
Advise patients that contact lenses should be removed before applying OXERVATE and to wait 15 minutes after instillation of the dose before reinserting the contact lenses into the eyes [see Dosage and Administration (2.2) and Warnings and Precautions (5.1)].

Use with other topical products
Advise the patient to administer the eye drops at least 15 minutes apart, if more than one topical ophthalmic product is being used to avoid diluting products. Administer OXERVATE 15 minutes prior to using any eye ointment, gel or other viscous eye drops.

Delayed or Missed Dose
If a dose is missed, treatment should be continued as normal, at the next scheduled administration.

Storage Information
Instruct the patient to remove the weekly carton(s) containing 7 OXERVATE vials from the insulated pack within 5 hours of receiving it from the pharmacy and store the weekly carton(s) in the refrigerator [36°F to 46°F (2°C to 8°C)].

Instruct the patient to only remove the number of OXERVATE vials from the weekly carton required for use over the course of a single day. Do not shake the vial.

Once opened, the vial can be kept in the original weekly carton in the refrigerator between 36°F to 46°F (2°C to 8°C) for up to 12 hours or at room temperature up to 77°F (25°C), but must be used within 12 hours. After 12 hours, advise patients to discard the vial with any unused amount.

Manufactured by
Dompé farmaceutici S.p.A.
Via Campo di Pile
67100 L’Aquila, Italy
U.S. License No. 2074

® 2024. Dompé U.S. Inc.

INSTRUCTIONS FOR USE

OXERVATE® (ox'-er-vayt)
(cenegermin-bkbj)
ophthalmic solution, for topical ophthalmic use

Read this Instructions for Use before you start using OXERVATE® and each time you get a refill. There may be new information. This leaflet does not take the place of talking to your doctor about your medical condition, or your treatment. Only you and your doctor can decide if OXERVATE is right for you. Share the important information in this leaflet with members of your household.

Important:

- OXERVATE is for use in the eye.
- Do not shake the OXERVATE vial.
- Use OXERVATE with the vial adapters, sterile disinfectant wipes, and pipettes that come with your Delivery System Kit.

OXERVATE is supplied in an insulated pack, in weekly cartons containing 7 multiple-dose vials. OXERVATE is supplied with an accompanying Delivery System Kit. The Delivery System Kit will have medical devices for withdrawing and using OXERVATE.

You will receive both the OXERVATE weekly carton(s) and the Delivery System Kit from the pharmacy.

The OXERVATE carton contains:

- 7 multiple-dose vials of OXERVATE (1 vial per day of the week)

The Delivery System Kit contains the following:

- 7 vial adapters
- 42 pipettes
- 42 sterile disinfectant wipes and
- Dose Recording Card (1)
- Extra adapter (1) pipettes (3) and wipes (3) are included as spares.

How should I store OXERVATE?

- Remove the weekly carton(s) of OXERVATE from the insulated pack and store it for up to 14 days in a refrigerator in the original carton as soon as you can.
- Store the weekly carton(s) at 36°F to 46°F (2°C to 8°C) no later than 5 hours from when you receive the medicine from your pharmacy. Do not freeze.
- OXERVATE is stored in a freezer at the pharmacy. If you start treatment right away after receiving the weekly carton, you will have to wait until the first vial is thawed. Thaw the vial at room temperature up to 77°F (25°C). Thawing the vial could take up to 30 minutes when kept at room temperature.
- Keep all medicines out of the reach of children.

Follow Steps 1 to 19 each day you use OXERVATE.

Gather your supplies:

- Remove 1 vial of OXERVATE from the refrigerator in the morning (always at the same time each morning) to use during the day. If OXERVATE is to be used in both eyes, remove 2 vials from the refrigerator.
- 1 vial adapter
- 1 pipette (if both eyes 2 pipettes)
- 1 sterile disinfectant wipe (if both eyes 2 sterile disinfectant wipes)
- Dose Recording Card

Step 1. Wash your hands.

Step 2. If you wear contact lenses, take them out before using OXERVATE.

Step 3. Remove the plastic flip-off cap from the vial.

Step 4. Peel-off the back of the vial adapter blister pack.

Step 5. Without removing the vial adapter from its blister pack, connect it to the vial by firmly pushing it down until it snaps into place over the neck of the vial. The spike of the vial adapter should pierce through the vial’s rubber stopper. After the vial adapter has been connected correctly, do not remove it from the vial.
Note: After the vial adapter is connected to the vial, OXERVATE can be stored in the refrigerator between 36°F to 46°F (2°C to 8°C) for up to 12 hours.
If needed, the OXERVATE with the connected vial adapter may be stored at room temperature up to 77°F (25°C).
Step 6. Remove and throw away the packaging of the vial adapter.

The multiple-dose vial of OXERVATE is now ready for use (1 drop in the affected eye every 2 hours six times a day).

To withdraw and give each dose of OXERVATE, follow Steps 7 to 19:

Step 7. Take a single sterile disinfectant wipe and gently clean the surface of the valve on the connector part of the vial adapter.
After cleaning, wait for about 1 minute to allow the valve to dry.

Step 8. Remove a pipette from its protective packaging.

Step 9. Screw the pipette (clockwise) into the connector part of the vial adapter.

Step 10. Make sure that the pipette plunger is pushed all the way down.

Step 11. Turn the vial upside-down with the pipette still connected. Gently pull the plunger until it stops, to draw the eye drop solution into the pipette. Make sure the plunger has reached the stop point.

Step 12. Check the pipette to make sure it contains the eye drop solution. Air bubbles may cause blockage and prevent the pipette from filling properly (especially the first time you withdraw the eye drop solution). If the pipette is empty, keep the vial with the connected pipette upside-down, push the plunger all the way in and pull it out again.

Step 13. After the pipette has been correctly filled, unscrew the pipette from the connector part of the vial adapter (counter-clockwise). Pull the pipette straight up to remove it.

Step 14.

- Sit or lie down to steady yourself when you instill OXERVATE.
- Holding the pipette, pointing down, between your middle finger and thumb, tilt your head back and position the pipette above your affected eye.
- With your other hand, pull down your lower eyelid, increasing the space between the inner eyelid and the eyeball (the conjunctival fornix).
- Gently push the plunger down until at least a drop is released into the conjunctival fornix.
- Make sure you do not touch your eye with the tip of the pipette.
- With your head still tilted back, blink a few times so that the medicine covers the surface of your eye.

Step 15. Throw away the used pipette right away after use, even if there is still some eye drop solution left in it.

Only use 1 pipette for each eye and each dose.

If you miss your eye and there is no longer any eye drop solution in the pipette, try again, using a new pipette and wipe (See Steps 7 to 14).

Step 16. After each use throughout the day, place the vial back in the refrigerator or keep it below 77°F (25°C) for the rest of the day, with the vial adapter still connected.

Step 17. Repeat from Step 7 to Step 16 every 2 hours 6 times a day, using a new sterile disinfectant wipe and a new pipette each time.

If you use drops in both eyes, repeat the above instructions for your other eye using a new pipette. You will need to use 2 vials each day.

Store the vial at or below 77ºF (25ºC) throughout the day. You can also store the vial in the refrigerator but do not freeze the vial.

Step 18. Throw away the used vial at the end of each day even if there is still some eye drop solution left in it. Throw away the vial no later than 12 hours from the time you connected the vial adapter to it even if there is eye solution still left in the vial.

Step 19. Track each time you instill an eye drop of OXERVATE on the weekly Dose Recording Card provided with the delivery system.

This will allow you to track your 6 doses each treatment day, the date of the first use of the weekly supply and the time of the vial opening (which is when you connect the vial adapter to the vial) during the week.

To make sure accurate dosing every 2 hours, you may want to set an alarm as a reminder for dosing.

Call your doctor for medical advice about side effects. You may report side effects to Dompé U.S. Inc. at 1-833-366-7387 or FDA at 1-800-FDA-1088 or www.fda.gov/medwatch.

Manufactured by:
Dompé farmaceutici S.p.A.
Via Campo di Pile
67100 L’Aquila, Italy
U.S. License No. 2074

Manufactured for: Dompé U.S. Inc.
400 S El Camino Real - Ste. 400, San Mateo, CA 94402

® 2024. Dompé U.S. Inc.

This Instructions for Use has been approved by the U.S. Food and Drug Administration.

Revised: December 2024.

PATIENT INFORMATION

OXERVATE® (ox'-er-vayt)

(cenegermin-bkbj)

ophthalmic solution, for topical ophthalmic use

What is OXERVATE®?

OXERVATE is a prescription eye drop solution used to treat a condition called neurotrophic keratitis.

OXERVATE is safe and effective in children two years of age and older.

Before you use OXERVATE, tell your doctor about all of your medical conditions, including if you:

- have an infection in your eye. If you get an eye infection while using OXERVATE, talk to your doctor right away.
- are using any other eye drops.
- wear contact lenses.
- are pregnant or plan to become pregnant. It is not known if OXERVATE will harm your unborn baby.
- are breastfeeding or plan to breastfeed. It is not known if OXERVATE passes into your breast milk. Talk to your doctor about the best way to feed your baby if you use OXERVATE.

Tell your doctor about all the medicines you take, including prescription and over-the-counter medicines, vitamins, and herbal supplements.

How should I use OXERVATE?

- See the complete Instructions for Use at the end of this Patient Information leaflet for detailed instructions about the right way to use OXERVATE.
- Use OXERVATE exactly as your doctor tells you.
- Use 1 drop of OXERVATE in the affected eye or both eyes if needed, 6 times each day, about 2 hours apart starting in the morning. Continue your treatment for 8 weeks.
- If you use any other eye drops, wait at least 15 minutes before or after using OXERVATE. This will help to avoid one eye drop diluting the other eye drop.
- If you also use an eye ointment or gel or an eye drop that is thick, use OXERVATE first, and then wait at least 15 minutes before using the other eye ointment, gel, or drops.
- If you wear contact lenses in your affected eye or both eyes remove them before using OXERVATE and wait 15 minutes after using OXERVATE before reinserting them.
- If you miss a dose of OXERVATE, take your next dose at your scheduled time. Do not take an extra dose to make up for a missed dose.
- Do not use other eye medicines without talking to your doctor.
- Talk to your doctor first before you stop using OXERVATE.
- If you have any questions about how to use OXERVATE, ask your doctor or pharmacist.

What should I avoid while using OXERVATE?

Your vision may be blurred for a short time after using OXERVATE. If this happens, wait until your vision clears before you drive or use machines.

What are the possible side effects of OXERVATE?

The most common side effects of OXERVATE are eye pain, enlarged blood vessels in the white of the eyes (ocular hyperemia), swelling (inflammation) of the eye, and increase of tears (increased lacrimation).

Tell your doctor if you have any side effects that bother you. These are not all the possible side effects of OXERVATE. Call your doctor for medical advice about side effects. You may report side effects to FDA at 1-800-FDA-1088.

General information about the safe and effective use of OXERVATE.

Medicines are sometimes prescribed for purposes other than those listed in a Patient Information leaflet. Do not use OXERVATE for a condition for which it was not prescribed. Do not give OXERVATE to other people, even if they have the same symptoms you have. It may harm them.

You can ask your pharmacist or doctor for information about OXERVATE that is written for health professionals.

What are the ingredients in OXERVATE?

Active ingredient: cenegermin-bkbj

Inactive ingredients: disodium hydrogen phosphate anhydrous, hydroxypropylmethyl cellulose, L‑methionine, mannitol, polyethylene glycol 6000, sodium dihydrogen phosphate dihydrate, trehalose dihydrate, Water for Injection, USP, and hydrochloric acid and/or sodium hydroxide to adjust pH.

Manufactured by:

Dompé farmaceutici S.p.A.

Via Campo di Pile

67100 L’Aquila, Italy

U.S. License No. 2074

Manufactured for: Dompé U.S. Inc.

400 S El Camino Real - Ste. 400, San Mateo, CA 94402

For more information, go to www.oxervate.com or call 1-833-366-7387.

This Patient Information has been approved by the U.S. Food and Drug Administration. Revised: December 2024

PRINCIPAL DISPLAY PANEL - Carton

NDC 71981-020-07

Oxervate® 0.002% (20 mcg/mL)
(cenegermin-bkbj) ophthalmic solution

7 X 1 mL multiple-dose vial

Sterile
For topical application in the eye

Rx only

PRINCIPAL DISPLAY PANEL- Delivery System Kit

NDC 71981-001-01

Delivery system kit for use with
Oxervate®

(cenegermin-bkbj ophthalmic solution)

Rx only

Dompé